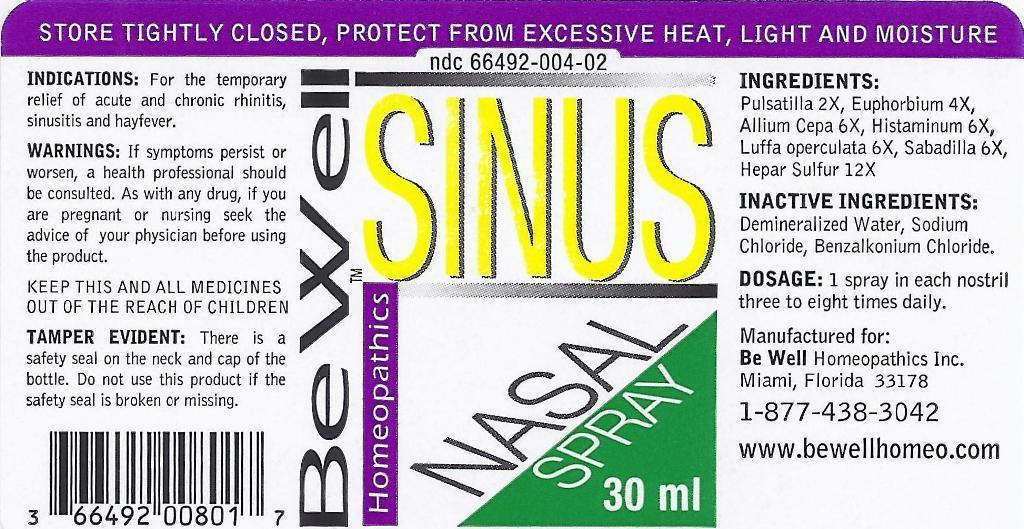 DRUG LABEL: SINUS
NDC: 66492-004 | Form: LIQUID
Manufacturer: Be Well Medical dba Richard Clement Nutrition y Be Well Homeopathics
Category: homeopathic | Type: HUMAN OTC DRUG LABEL
Date: 20211229

ACTIVE INGREDIENTS: PULSATILLA VULGARIS 2 [hp_X]/1 mL; EUPHORBIA RESINIFERA RESIN 4 [hp_X]/1 mL; ONION 6 [hp_X]/1 mL; HISTAMINE DIHYDROCHLORIDE 6 [hp_X]/1 mL; LUFFA OPERCULATA FRUIT 6 [hp_X]/1 mL; SCHOENOCAULON OFFICINALE SEED 6 [hp_X]/1 mL; CALCIUM SULFIDE 12 [hp_X]/1 mL
INACTIVE INGREDIENTS: WATER; SODIUM CHLORIDE; BENZALKONIUM CHLORIDE

SINUS NASAL SPRAY

ACTIVE INGREDIENTS:

Pulsatilla 2X, Euphorbium 4X, Allium Cepa 6X, Histaminum 6X, Luffa Operculata 6X, Sabadilla 6X, Hepar Sulfur 12X

INDICATIONS AND USAGE

INDICATIONS: For the temporary relief of acute and chronic rhinitis, sinusitis and hayfever.

WARNINGS:

If symptoms persist or worsen, a health professional should be consulted. As with any drug, if you are pregnant or nursing seek the advice of your physician before using the product.

KEEP THIS AND ALL MEDICINES OUT OF THE REACH OF CHILDREN.

Keep out of reach of children.

DOSAGE AND ADMINISTRATION

DOSAGE: 1 spray in each nostril three to eight times daily.

OTHER SAFETY INFORMATION

TAMPER EVIDENT: There is a safety seal on the neck and cap of the bottle. Do not use this product if the safety seal is broken or missing.

Store tightly closed, protect from excessive heat, light and moisture.

INACTIVE INGREDIENT

INACTIVE INGREDIENTS: Demineralized Water, Sodium Chloride, Benzalkonium Chloride.

QUESTIONS

Manufactured for:

Be Well Homeopathics Inc.

Miami, Florida 33178

1-877-438-3042

www.bewellhomeo.com

PACKAGE LABEL

NDC 66492-004-02

Be Well Homeopathics™

SINUS NASAL SPRAY

30 ml

PURPOSE

Temporary relief of acute and chronic rhinitis, sinusitis and hayfever.